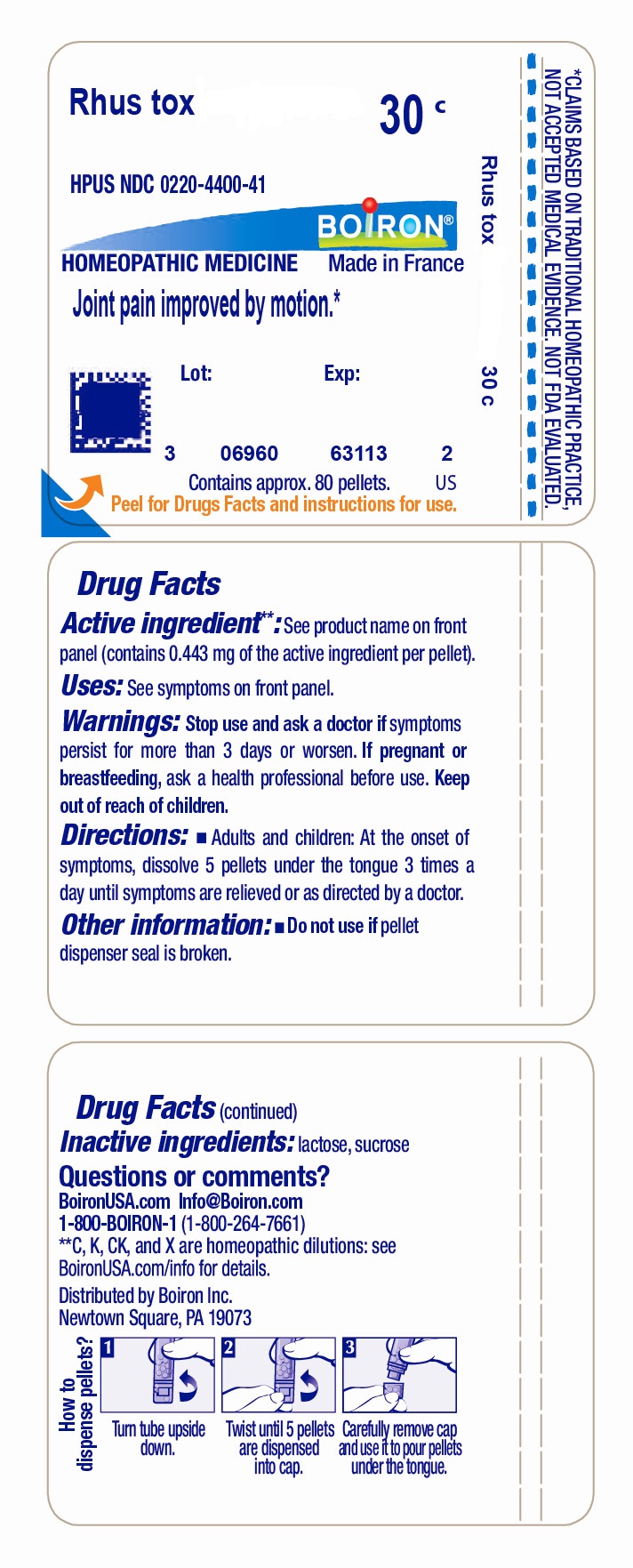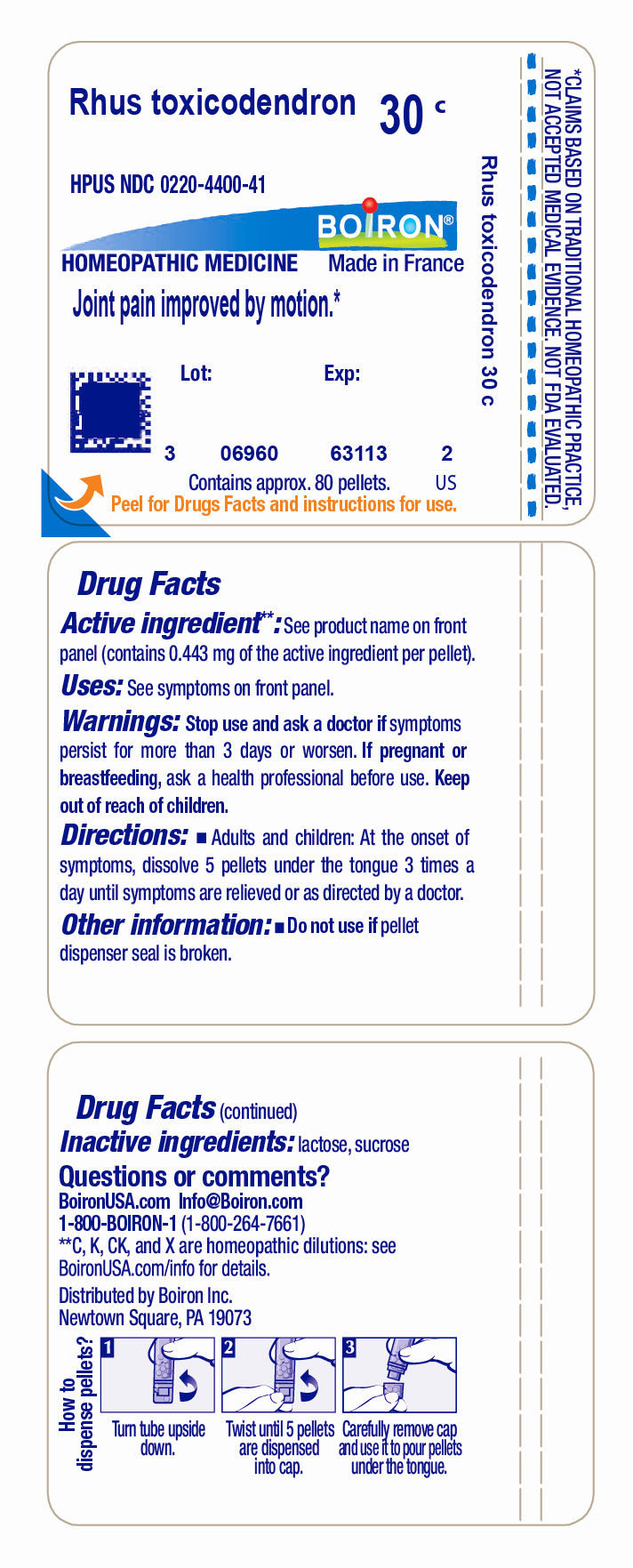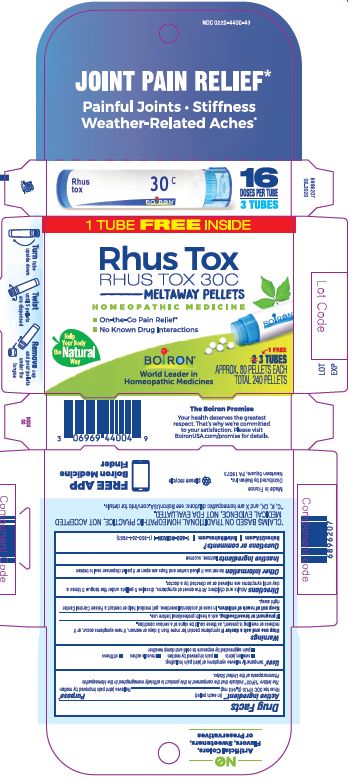 DRUG LABEL: Rhus tox
NDC: 0220-4400 | Form: PELLET
Manufacturer: Boiron
Category: homeopathic | Type: HUMAN OTC DRUG LABEL
Date: 20230620

ACTIVE INGREDIENTS: TOXICODENDRON PUBESCENS LEAF 30 [hp_C]/30 [hp_C]
INACTIVE INGREDIENTS: LACTOSE, UNSPECIFIED FORM; SUCROSE

Rhus tox 30C

ACTIVE INGREDIENT

Tube - Rhus tox 30C (**contains 0.443 mg of the active ingredient per pellet)

Box - Rhus tox 30C HPUS (**contains 0.443 mg of the active ingredient in each pellet)

The letters "HPUS" indicate that the components in this product are officially monographed in the Homeopathic Pharmacopoeia of the United States.

PURPOSE

Box - Relieves joint pain improved by motion*

INDICATIONS AND USAGE

Tube - Joint Pain Improved By Motion*

Box - temporarily relieves symptoms of joint pain including: swollen joints, pain improved by motion, muscle aches, stiffness, pain aggravated by exposure to cold and damp weather

STOP USE

Tube - Stop use and ask a doctor if symptoms persist for more than 3 days or worsen.

Box - Stop use and ask a doctor if symptoms persist for more than 3 days or worsen, if new symptoms occur, or if redness or swelling is present, as these could be signs of a serious condition.

PREGNANCY OR BREAST FEEDING

Tube - If pregnant or breast-feeding, ask a health professional before use.

Box - If pregnant or breast-feeding, ask a health professional before use.

Tube - Keep out of reach of children.

Box - Keep out of reach of children. In case of accidental overdose, get medical help or contact a Poison Control Center right away.

Tube - Do not use if pellet dispenser seal is broken.
Contains approx 80 pellets.
How to dispense pellets? Turn tube upside down. Twist until 5 pellets are dispensed into cap. Carefully remove the cap and use it to pour pellets under the tongue.
*CLAIMS BASED ON TRADITIONAL HOMEOPATHIC PRACTICE NOT ACCEPTED MEDICAL EVIDENCE. NOT FDA EVALUATED.
*C,K,CK, and X are homeopathic dilutions: see BoironUSA.com/info for details.

Box - Do not use if glued carton end flaps are open or if pellet dispenser seal is broken.

3 Tubes approx 80 pellets 16 Doses per tube Total 240 pellets

How to dispense pellets? Turn tube upside down. Twist until 5 pellets are dispensed. Remove cap and pour pellets under the tongue.

No known drug interactions

On-the-go pain relief*

Meltaway Pellets
*CLAIMS BASED ON TRADITIONAL HOMEOPATHIC PRACTICE NOT ACCEPTED MEDICAL EVIDENCE. NOT FDA EVALUATED.
*C,K,CK, and X are homeopathic dilutions: see BoironUSA.com/info for details.

INACTIVE INGREDIENT

Tube - lactose, sucrose

Box - lactose, sucrose

DOSAGE AND ADMINISTRATION

Tube - Adults and children: At the onset of symptoms, dissolve 5 pellets under the tongue 3 times a day until symptoms are relieved or as directed by a doctor.

Box - Adults and children 12 years of age and older: At the onset of symptoms, dissolve 5 pellets under the tongue 3 times a day until symptoms are relieved or as directed by a doctor.

QUESTIONS

Tube - 1-800-BOIRON-1 (1-800-264-7661),

BoironUSA.com Info@boiron.com
Distributed by Boiron, Inc. Newtown Square, PA 19073

Box - 1-800-BOIRON-1 (1-800-264-7661),

BoironUSA.com Info@boiron.com
Distributed by Boiron, Inc. Newtown Square, PA 19073